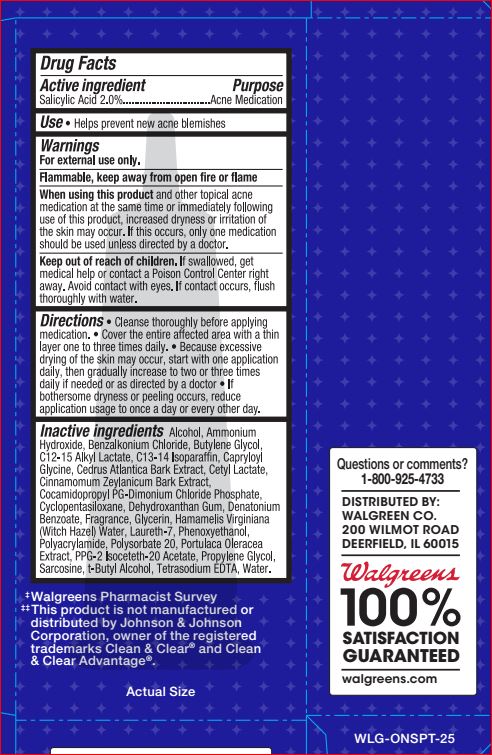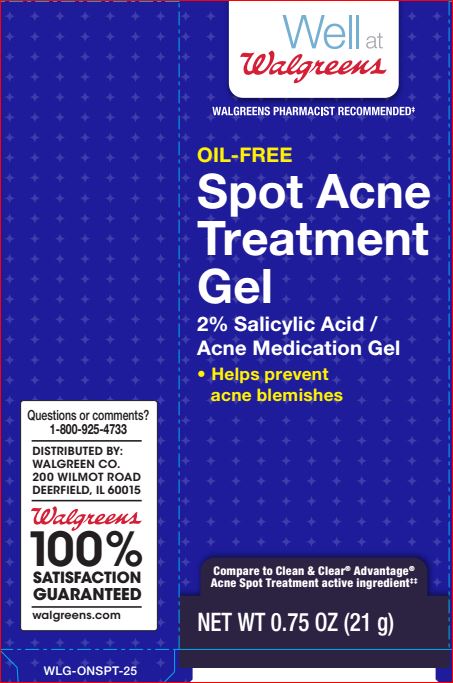 DRUG LABEL: Spot Acne Treatment
NDC: 0363-7782 | Form: GEL
Manufacturer: Walgreens
Category: otc | Type: HUMAN OTC DRUG LABEL
Date: 20180430

ACTIVE INGREDIENTS: Salicylic Acid 2 g/100 g
INACTIVE INGREDIENTS: Alcohol; AMMONIA; Benzalkonium Chloride; Butylene Glycol; C12-15 Alkyl Lactate; C13-14 Isoparaffin; Capryloyl Glycine; CEDRUS ATLANTICA BARK; Cetyl Lactate; CINNAMON BARK OIL; Cocamidopropyl PG-Dimonium Chloride Phosphate; CYCLOMETHICONE 5; Dehydroxanthan Gum; Denatonium Benzoate; Glycerin; HAMAMELIS VIRGINIANA TOP WATER; Laureth-7; Phenoxyethanol; Polysorbate 20; PURSLANE; PPG-2 Isoceteth-20 Acetate; Propylene Glycol; Sarcosine; TERT-BUTYL ALCOHOL; EDETATE SODIUM; WATER

Well at Walgreens
Drug Facts

Active ingredients Purpose

Salicylic Acid - 2.0% Acne Medication

Use

Helps prevent new acne blemishes

For external use only Flammable, keep away from oipen fire or flame

When using this product skin irritation and dryness is more likely occur if you use another topical acne medication at the same time. If irritation occurs, only use one topical acne medication at a time.

Keep out of reach of the children
If product is swallowed, get medical help or contact a Poison Control Center right away

Avoid contact with eyes. If contact occurs, flush thoroughly with water

Directions

Cleanse thoroughly before applying treatment
Cover the entire affected area with a thin layer one to three times daily.
Because of excessive drying of the skin may occurs, start with one application daily, then gradually increase to two or three times daily if needed or as directed by a doctor.
If bothersome dryness or peeling occurs, reduce application usage to once a day or every other day.

Inactive ingredients

Alcohol
Ammonium Hydroxide
Benzalkonium Chloride
Butylene Glycol
C12-15 Alkyl Lactate
C13-14 Isoparaffin
Capryloyl Glycine
Cedrus Atlantica Bark Extract
Cetyl Lactate
Cinnamomum Zeylanicum Bark Extract
Cocamidopropyl PG-Dimonium Chloride Phosphate
Cyclopentasiloxane
Dehydroxanthan Gum
Denatonium Benzoate
Fragrance
Glycerin
Hamamelis Virginiana (Witch Hazel) Water
Laureth-7
Phenoxyethanol
Polyacrylamide
Polysorbate 20
Portulaca Oleracea Extract
PPG-2 Isoceteth-20 Acetate
Propylene Glycol
Sarcosine
t-Butyl Alcohol
Tetrasodium EDTA
Water